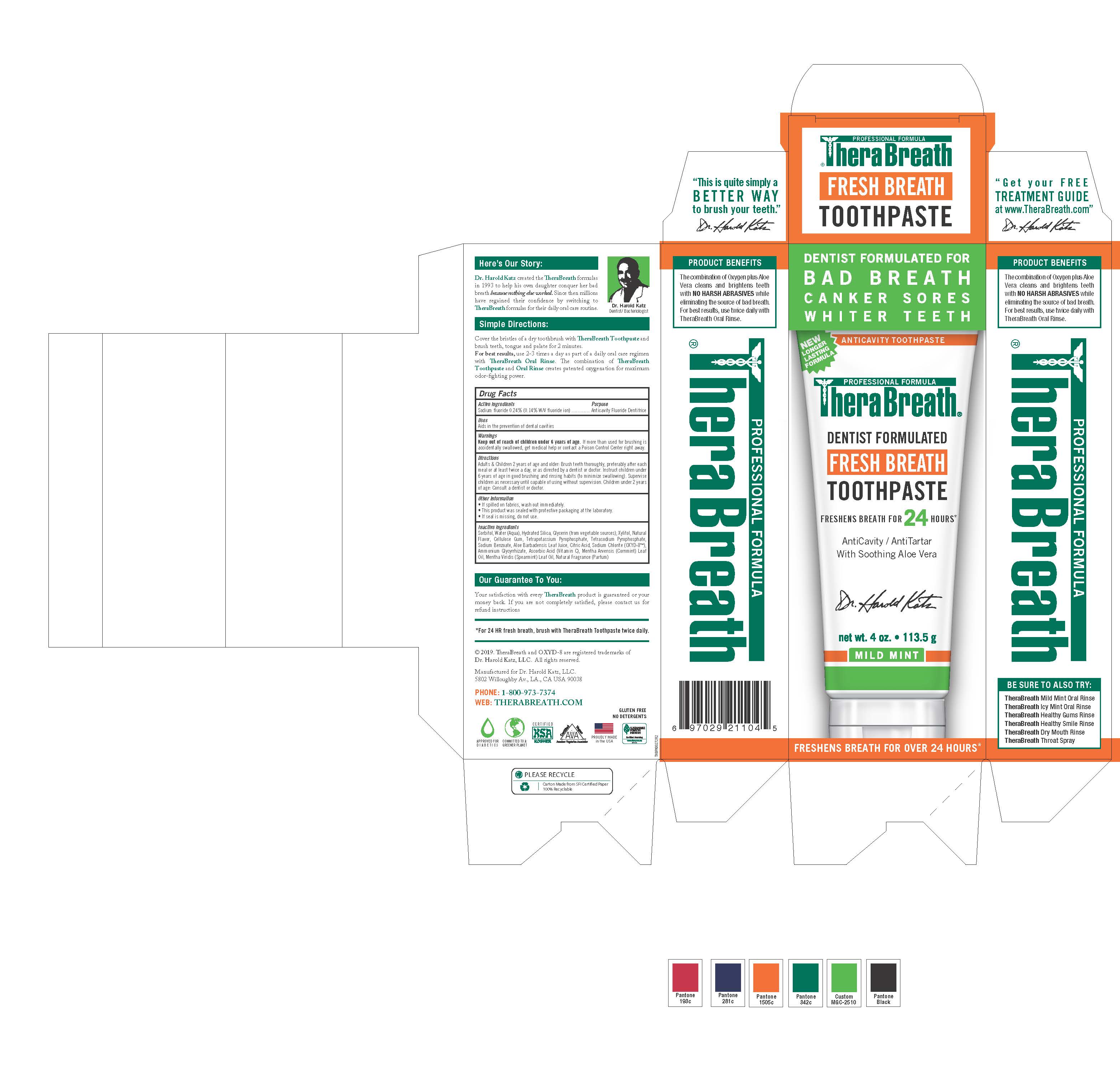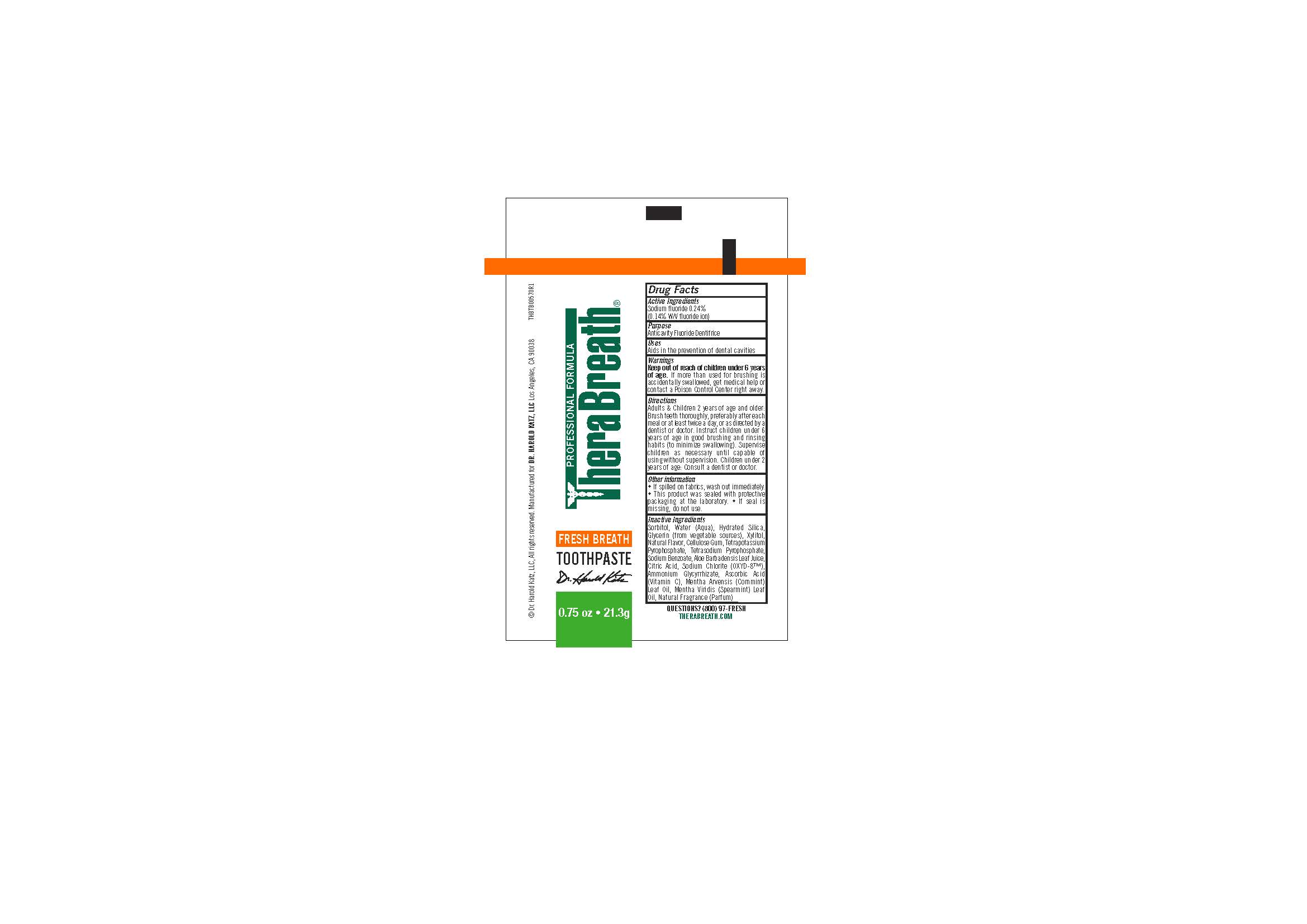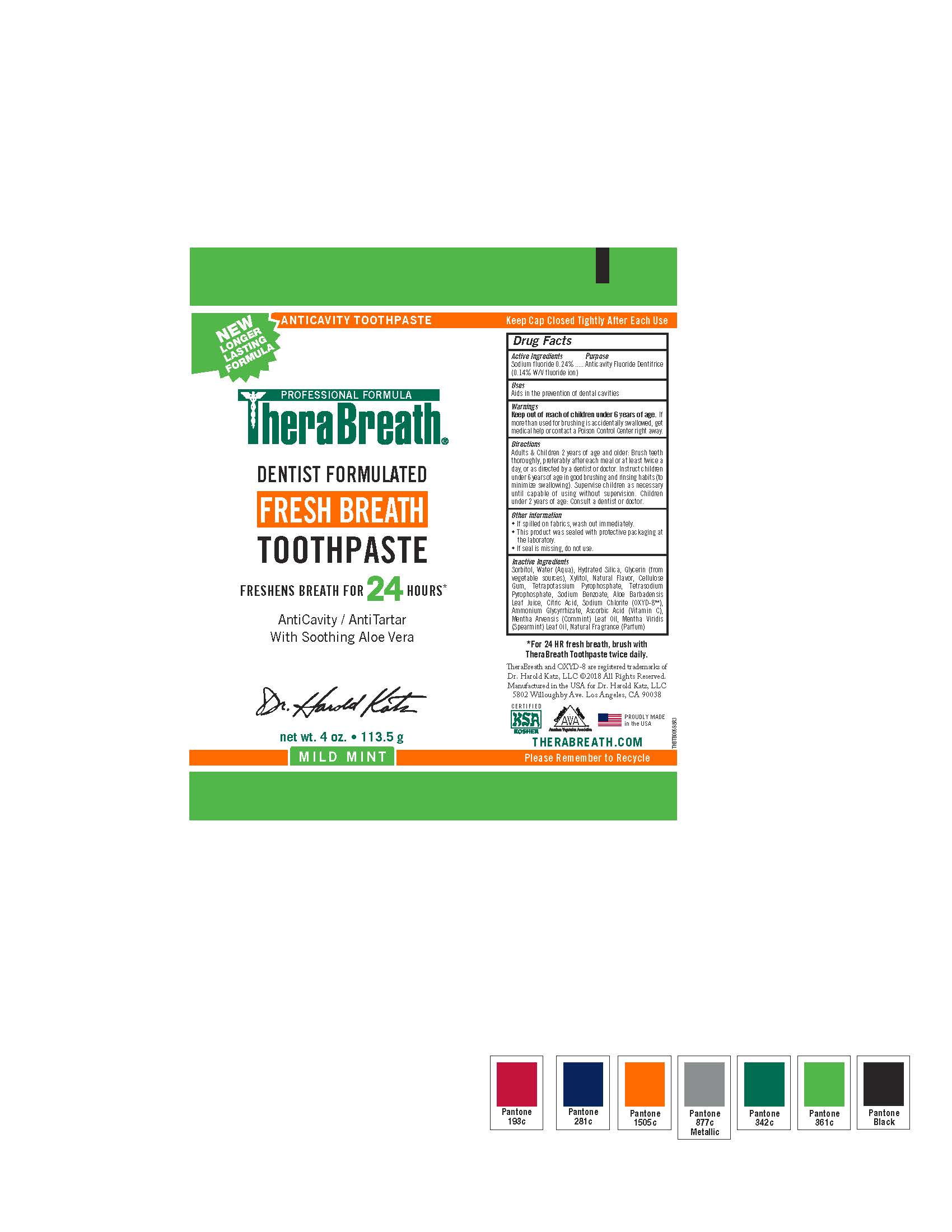 DRUG LABEL: TheraBreath Fresh Breath
NDC: 72551-250 | Form: PASTE, DENTIFRICE
Manufacturer: Dr. Harold Katz, LLC
Category: otc | Type: HUMAN OTC DRUG LABEL
Date: 20220204

ACTIVE INGREDIENTS: SODIUM FLUORIDE 0.0024 g/1 g
INACTIVE INGREDIENTS: SPEARMINT; MENTHA ARVENSIS FLOWER OIL; ASCORBIC ACID; AMMONIUM GLYCYRRHIZATE; SODIUM CHLORITE; ALOE VERA LEAF; SODIUM BENZOATE; POTASSIUM PYROPHOSPHATE; SODIUM PYROPHOSPHATE; CARBOXYMETHYLCELLULOSE SODIUM, UNSPECIFIED FORM; XYLITOL; GLYCERIN; HYDRATED SILICA; WATER; SORBITOL

TheraBreath Fresh Breath

Active Ingredients

Sodium Fluoride 0.24%

(0.14% W/V fluoride ion)

Purpose

Anticavity Fluoride Dentrifice

Uses

Aids in the prevention of dental cavities

Directions

Adults & Children 2 years of age and older: Brush teeth thoroughly, preferably after each meal or at least twice a day, or as directed by a dentist or doctor. Instruct children under 6 years of age in good brushing and rinsing habits (to minimize swallowing). Supervise children as necessary until capable of using without supervision. Children under 2 years of age: Consult a dentist or doctor.

Warnings

If more than used for brushing is accidentally swallowed, get medical help or contact a Poison Control Center right away.

Warnings

Keep out of reach of children under 6 years of age.

Other information

- If spilled on fabrics, wash out immediately.
- This product was sealed with protective packaging at the laboratory.
- If seal is missing, do not use.

Inactive Ingredients

Sorbitol, Water (Aqua), Hydrated Silica, Glycerin (from vegetable sources), Xylitol, Natural Flavor, Cellulose Gum, Tetrapotassium Pyrophosphate, Tetrasodium Pyrophosphate, Sodium Benzoate, Aloe Barbadensis Leaf Juice, Citric Acid, Sodium Chlorite (OXYD-8™), Ammonium Glycyrrhizate, Ascorbic Acid (Vitamin C), Mentha Arvensis (Cornmint) Leaf Oil, Mentha Viridis (Spearmint) Leaf Oil, Natural Fragrance (Parfum)